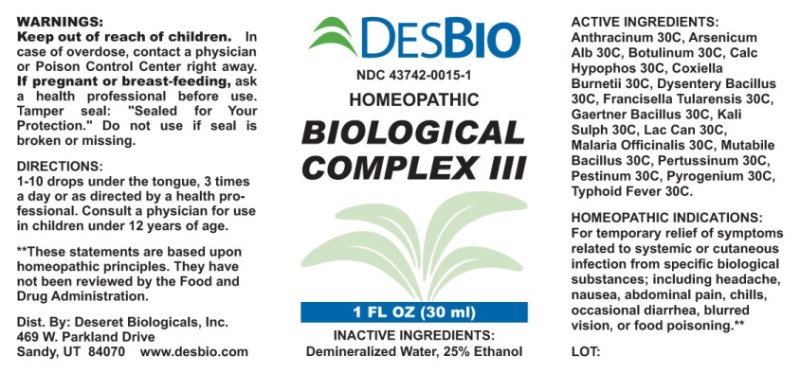 DRUG LABEL: Biological Complex
NDC: 43742-0015 | Form: LIQUID
Manufacturer: Deseret Biologicals, Inc.
Category: homeopathic | Type: HUMAN OTC DRUG LABEL
Date: 20181024

ACTIVE INGREDIENTS: BACILLUS ANTHRACIS IMMUNOSERUM RABBIT 30 [hp_C]/1 mL; ARSENIC TRIOXIDE 30 [hp_C]/1 mL; BOTULINUM TOXIN TYPE A 30 [hp_C]/1 mL; CALCIUM HYPOPHOSPHITE 30 [hp_C]/1 mL; COXIELLA BURNETII 30 [hp_C]/1 mL; SHIGELLA DYSENTERIAE 30 [hp_C]/1 mL; FRANCISELLA TULARENSIS 30 [hp_C]/1 mL; SALMONELLA ENTERICA SUBSP. ENTERICA SEROVAR ENTERITIDIS 30 [hp_C]/1 mL; POTASSIUM SULFATE 30 [hp_C]/1 mL; CANIS LUPUS FAMILIARIS MILK 30 [hp_C]/1 mL; PLASMODIUM MALARIAE 30 [hp_C]/1 mL; ESCHERICHIA COLI 30 [hp_C]/1 mL; HUMAN SPUTUM, BORDETELLA PERTUSSIS INFECTED 30 [hp_C]/1 mL; YERSINIA PESTIS 30 [hp_C]/1 mL; RANCID BEEF 30 [hp_C]/1 mL; SALMONELLA ENTERICA SUBSP. ENTERICA SEROVAR TYPHI 30 [hp_C]/1 mL
INACTIVE INGREDIENTS: WATER; ALCOHOL

Drug Facts:

ACTIVE INGREDIENTS:

Anthracinum 30C, Arsenicum Album 30C, Botulinum 30C, Calcarea Hypophosphorosa 30C, Coxiella Burnetii 30C, Dysentery Bacillus 30C, Francisella Tularensis 30C, Gaertner Bacillus 30C, Kali Sulphuricum 30C, Lac Caninum 30C, Malaria Officinalis 30C, Mutabile Bacillus 30C, Pertussinum 30C, Pestinum 30C, Pyrogenium 30C, Typhoid Fever 30C.

HOMEOPATHIC INDICATIONS:

For temporary relief of symptoms related to systemic or cutaneous infection from specific biological substances; including headache, nausea, abdominal pain, chills, occasional diarrhea, blurred vision, or food poisoning.**

**These statements are based upon traditional homeopathic principles. They have not been reviewed by the Food and Drug Administration.

WARNINGS:

Keep out of reach of children. In case of overdose, contact physician or Poison Control Center right away.

If pregnant or breast-feeding, ask a health professional before use.

Tamper seal: "Sealed for Your Protection." Do not use if seal is broken or missing.

DIRECTIONS:

1-10 drops under the tongue, 3 times a day or as directed by a health professional. Consult a physician for use in children under 12 years of age.

INACTIVE INGREDIENTS:

Demineralized Water, 25% Ethanol.

KEEP OUT OF REACH OF CHILDREN:

Keep out of the reach of children. In case of overdose, contact physician or Poison Control Center right away.

HOMEOPATHIC INDICATIONS:

For temporary relief of symptoms related to systemic or cutaneous infection from specific biological substances; including headache, nausea, abdominal pain, chills, occasional diarrhea, blurred vision, or food poisoning.**

**These statements are based upon traditional homeopathic principles. They have not been reviewed by the Food and Drug Administration.

QUESTIONS:

Dist. By: Deseret Biologicals, Inc.

469 W. Parkland Drive

Sandy, UT 84070

www.desbio.com

PACKAGE LABEL

DESBIO
NDC 43742-0015-1
HOMEOPATHIC
BIOLOGICAL
COMPLEX III
1 FL OZ (30 ml)